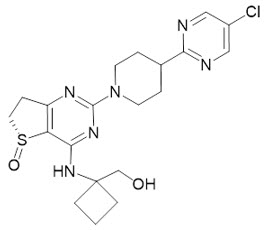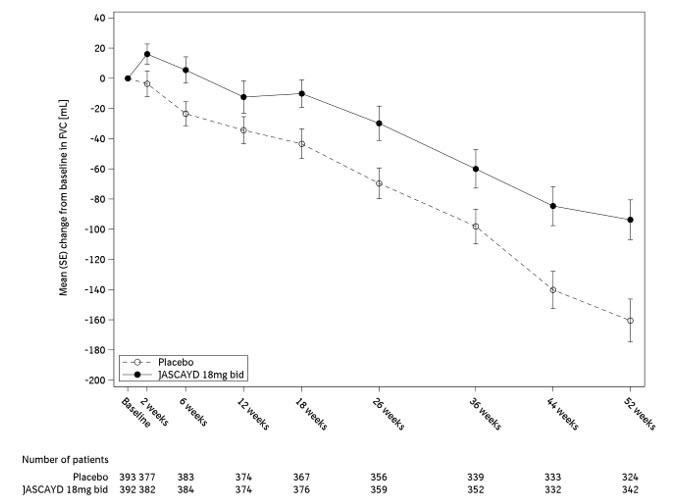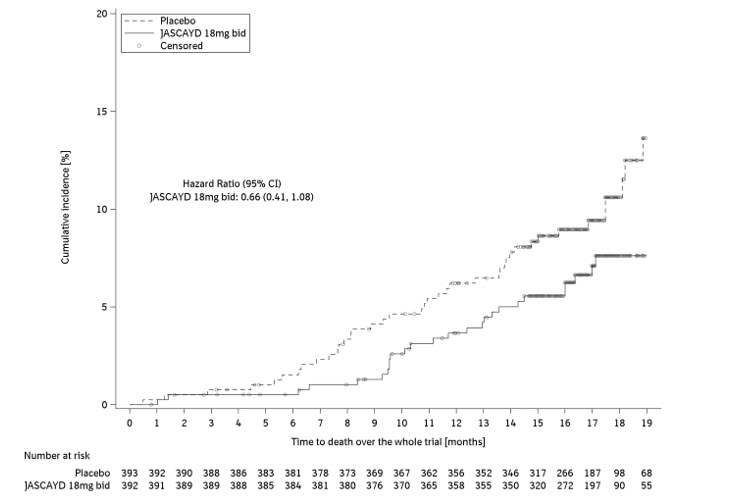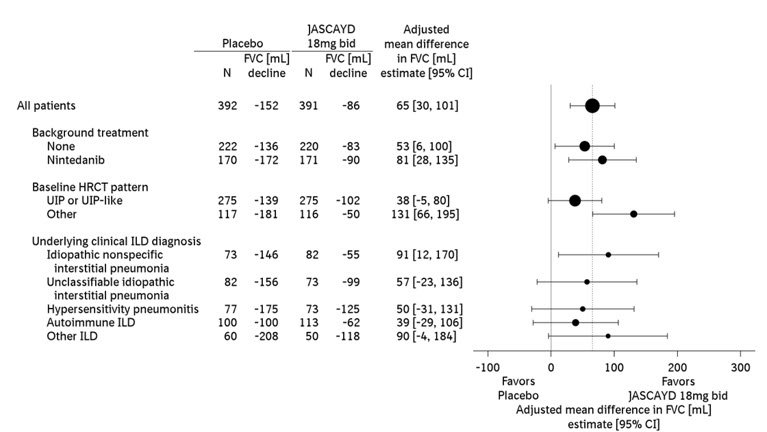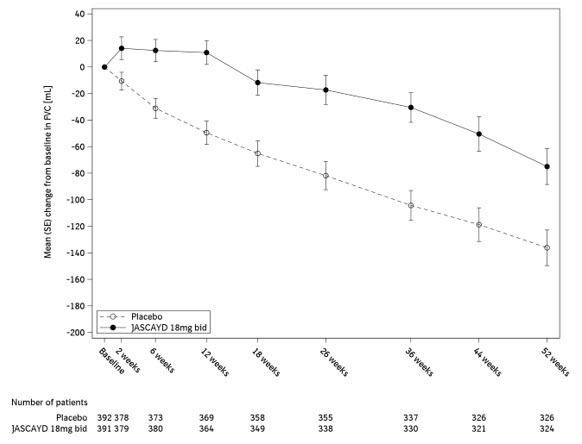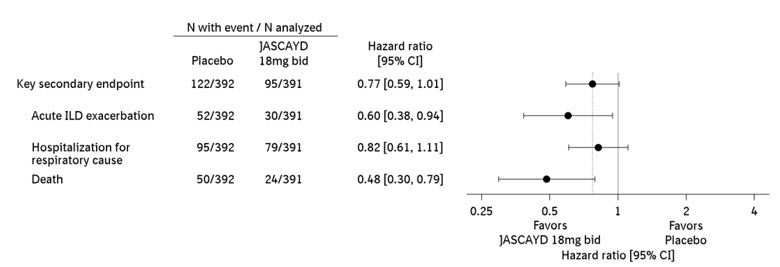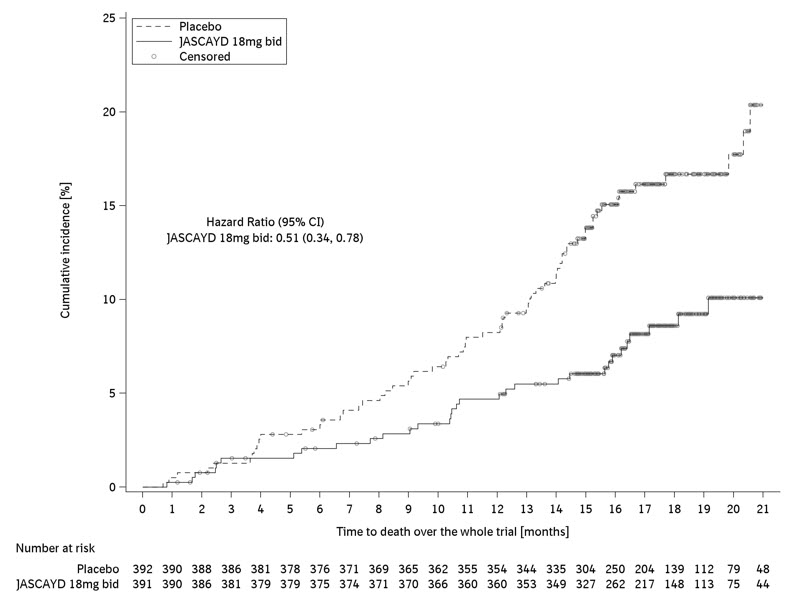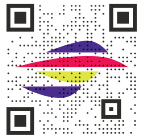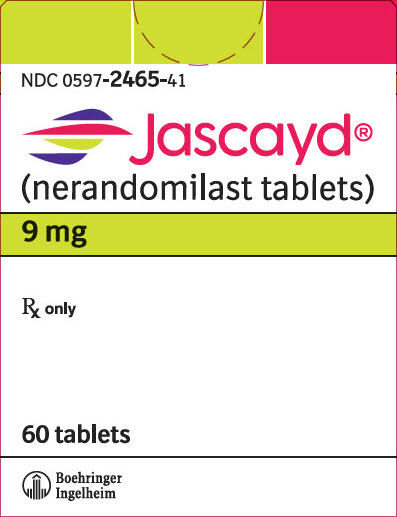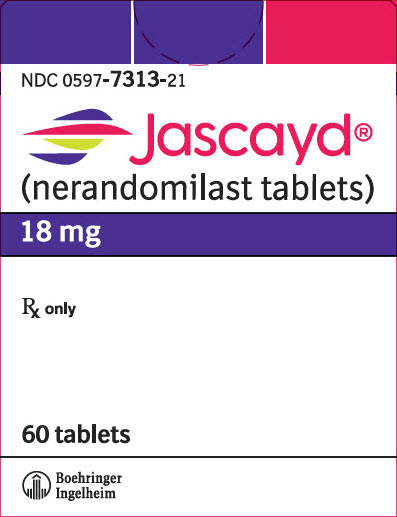 DRUG LABEL: JASCAYD
NDC: 0597-2465 | Form: TABLET, FILM COATED
Manufacturer: Boehringer Ingelheim Pharmaceuticals, Inc.
Category: prescription | Type: HUMAN PRESCRIPTION DRUG LABEL
Date: 20260202

ACTIVE INGREDIENTS: NERANDOMILAST 9 mg/1 1

HIGHLIGHTS OF PRESCRIBING INFORMATION

These highlights do not include all the information needed to use JASCAYD safely and effectively. See full prescribing information for JASCAYD.
JASCAYD® (nerandomilast tablets), for oral use
Initial U.S. Approval: 2025

RECENT MAJOR CHANGES

Indications and Usage, Progressive Pulmonary Fibrosis (1.2) | 12/2025

1 INDICATIONS AND USAGE

JASCAYD is a phosphodiesterase 4 (PDE4) inhibitor indicated for:

- The treatment of idiopathic pulmonary fibrosis in adult patients. (1.1)
- The treatment of progressive pulmonary fibrosis in adult patients. (1.2)

2 DOSAGE AND ADMINISTRATION

- Recommended Dosage: 18 mg orally twice daily approximately 12 hours apart with or without food. (2.1)
- Reduce JASCAYD to 9 mg twice daily for patients who are unable to tolerate 18 mg twice daily, except in patients taking concomitant pirfenidone. (2.1, 7.1)
- Swallow tablets whole or dispersed in water. (2.1)
- See full prescribing information for dosage modification for concomitant use with CYP3A inhibitors and administration instructions for patients who have difficulty swallowing tablets. (2.2, 2.3)

3 DOSAGE FORMS AND STRENGTHS

Tablets: 9 mg and 18 mg (3)

4 CONTRAINDICATIONS

None. (4)

6 ADVERSE REACTIONS

Most common adverse reactions (≥5%) are diarrhea, COVID-19, upper respiratory tract infection, depression, weight decreased, decreased appetite, nausea, fatigue, headache, vomiting, back pain, and dizziness. (6.1)

To report SUSPECTED ADVERSE REACTIONS, contact Boehringer Ingelheim Pharmaceuticals, Inc. at (800) 542-6257 or FDA at 1-800-FDA-1088 or www.fda.gov/medwatch.

7 DRUG INTERACTIONS

Strong CYP3A Inhibitors: Reduce JASCAYD dosage to 9 mg twice daily. (2.2, 7.1)

Moderate or Strong CYP3A Inducers: Avoid concomitant use with JASCAYD. (7.1)

FULL PRESCRIBING INFORMATION

1 INDICATIONS AND USAGE

1.1 Idiopathic Pulmonary Fibrosis

JASCAYD is indicated for the treatment of idiopathic pulmonary fibrosis (IPF) in adult patients.

1.2 Progressive Pulmonary Fibrosis

JASCAYD is indicated for the treatment of progressive pulmonary fibrosis (PPF) in adult patients.

2 DOSAGE AND ADMINISTRATION

2.1 Recommended Dosage

The recommended dosage of JASCAYD is 18 mg twice daily, administered orally (swallow tablets whole or dispersed in water) approximately 12 hours apart, with or without food.

- Reduce JASCAYD to 9 mg twice daily for patients who are unable to tolerate 18 mg twice daily, except in patients who concomitantly use JASCAYD with pirfenidone.

Recommended Dosage for Concomitant Use with Pirfenidone

Recommended dosage of JASCAYD is 18 mg twice daily when used concomitantly with pirfenidone. Do not reduce dosage to 9 mg twice daily [see Drug Interactions (7.1)].

Administration Instructions

Swallow JASCAYD tablets whole or dispersed in water [see Dosage and Administration (2.3) and Clinical Pharmacology (12.3)].

Missed Dose(s)

If a dose of JASCAYD is missed, advise the patient to take the next dose at the next scheduled time. Advise the patient to not make up for a missed dose.

Maximum Recommended Dosage

The maximum recommended dosage of JASCAYD is 18 mg twice daily.

2.2 Dosage Modification of JASCAYD for Concomitant Use With CYP3A Inhibitors

Strong CYP3A Inhibitors

Reduce JASCAYD dosage to 9 mg twice daily when used concomitantly with strong CYP3A inhibitors [see Drug Interactions (7.1)].

Moderate and Weak CYP3A Inhibitors

No dosage modification is recommended for JASCAYD when used concomitantly with moderate or weak CYP3A inhibitors.

2.3 Administration Instructions for Patients Who Have Difficulty Swallowing Tablets

Disperse JASCAYD tablet in water and administer as follows:

- Place approximately 100 mL (3 to 4 ounces) of non-carbonated, room temperature water in a glass. Do not use any other liquids.
- Place a JASCAYD tablet in the water, without crushing, and stir regularly for approximately 15 to 20 minutes until the tablet is dispersed into very small pieces (the tablet will not completely dissolve).
- Drink the dispersion within 2 hours of mixing.
- If the dispersion is not drunk immediately, stir again before drinking.
- Rinse the glass with approximately 100 mL (3 to 4 ounces) of water and drink to ensure the full dose is administered.

3 DOSAGE FORMS AND STRENGTHS

Tablets:

- 9 mg, light yellow, oval, biconvex, film-coated tablets debossed with the Boehringer Ingelheim company symbol on one side and "F9" on the other side.
- 18 mg, light red, oval, biconvex, film-coated tablets debossed with the Boehringer Ingelheim company symbol on one side and "F18" on the other side.

4 CONTRAINDICATIONS

None.

6 ADVERSE REACTIONS

6.1 Clinical Trials Experience

Because clinical trials are conducted under widely varying conditions, adverse reaction rates observed in the clinical trials of a drug cannot be directly compared to rates in clinical trials of another drug and may not reflect the rates observed in practice.

Adverse Reactions for Idiopathic Pulmonary Fibrosis

The safety of JASCAYD was based on a randomized, placebo-controlled, double-blind trial (FIBRONEER-IPF), which included 1,177 adult patients with IPF who were randomized in a 1:1:1 ratio to receive JASCAYD 9 mg twice daily, JASCAYD 18 mg twice daily, or matching placebo. Patients received JASCAYD or placebo with or without background antifibrotic treatment (nintedanib or pirfenidone) for at least 52 weeks [see Clinical Studies (14.1)]. The median duration of exposure was 14 months in each treatment arm.

Discontinuation due to adverse reactions occurred more frequently in patients treated with JASCAYD (with or without background antifibrotic treatment) 18 mg (15%) and 9 mg (12%) compared to placebo (11%). The most frequent adverse reaction leading to discontinuation of JASCAYD 18 mg and 9 mg was diarrhea (6% and 2%, respectively).

Table 1 lists the most common adverse reactions from the studied population with an incidence of greater than or equal to 5% in JASCAYD-treated patients and more common than the placebo group.

Table 1 Adverse Reactions with JASCAYD with Incidence of ≥5% and More Common than Placebo in Patients^1 with IPF (FIBRONEER-IPF Trial)
 | JASCAYD 18 mg BID n=392 | JASCAYD 9 mg BID n=392 | Placebo n=393
Diarrhea | 42% | 31% | 17%
COVID-19 | 13% | 16% | 12%
Upper respiratory tract infection | 13% | 11% | 10%
Depression^2 | 12% | 11% | 10%
Weight decreased | 11% | 10% | 8%
Decreased appetite | 9% | 9% | 5%
Nausea | 8% | 9% | 7%
Fatigue | 7% | 8% | 6%
Headache | 7% | 6% | 5%
Vomiting | 6% | 5% | 5%
Back pain | 6% | 5% | 4%
Dizziness | 5% | 6% | 5%
^1Studied population including patients who received JASCAYD with or without background antifibrotic treatment (nintedanib or pirfenidone)
^2Includes depression, depressed mood, depression rating scale score increased, suicidal ideation, adjustment disorder with depressed mood, depressive symptom
BID: twice daily; COVID-19: infection with SARS-CoV-2 virus

Specific Adverse Reactions of JASCAYD for IPF with or without Concomitant Use of Nintedanib or Pirfenidone

Diarrhea

Diarrhea was more common in patients using JASCAYD with concomitant nintedanib. In patients taking nintedanib, diarrhea occurred in 62%, 50%, and 28% of patients treated with JASCAYD 18 mg twice daily, JASCAYD 9 mg twice daily, and placebo, respectively. In patients using concomitant pirfenidone, diarrhea occurred in 24% and 8% of patients treated with JASCAYD 18 mg twice daily and placebo, respectively. In patients without concomitant antifibrotic treatment, diarrhea occurred in 26%, 17%, and 8% of patients using JASCAYD 18 mg twice daily, JASCAYD 9 mg twice daily, and placebo, respectively.

Diarrhea was the most common adverse reaction associated with treatment discontinuation, and most common with JASCAYD used concomitantly with nintedanib: discontinuation occurred in 13%, 2%, and 1% of patients treated with JASCAYD 18 mg twice daily, JASCAYD 9 mg twice daily and placebo, respectively. No treatment discontinuations due to diarrhea occurred in patients treated with background pirfenidone and JASCAYD 18 mg twice daily or background pirfenidone with placebo. Diarrhea leading to treatment discontinuation occurred in 1% of patients treated with JASCAYD 18 mg twice daily and in no patients treated with JASCAYD 9 mg or placebo without concomitant antifibrotic treatment.

In most patients treated with JASCAYD, diarrhea was of mild to moderate intensity and generally occurred within the first 3 months of treatment.

Weight Decrease

Weight decrease was most common in patients who received JASCAYD concomitantly with nintedanib in the studied population: in patients taking nintedanib, weight decrease occurred in 16%, 14%, and 12% of patients treated with JASCAYD 18 mg twice daily, JASCAYD 9 mg twice daily, and placebo, respectively. In patients using concomitant pirfenidone, weight decrease occurred in 6% and 5% of patients treated with JASCAYD 18 mg twice daily and placebo, respectively. In patients without background antifibrotic therapy, weight decrease occurred in 8%, 2%, and 6% of patients treated with JASCAYD 18 mg twice daily, JASCAYD 9 mg twice daily, and placebo, respectively.

Decreased Appetite

In patients taking nintedanib, decreased appetite occurred in 7%, 10%, and 4% in JASCAYD 18 mg twice daily, JASCAYD 9 mg twice daily, and placebo, respectively. In patients using concomitant pirfenidone, decreased appetite occurred in 13% and 10% of patients treated with JASCAYD 18 mg twice daily and placebo, respectively. In patients without concomitant antifibrotic treatment, decreased appetite occurred in 9%, 6%, and 0% of patients treated with JASCAYD 18 mg twice daily, JASCAYD 9 mg twice daily, and placebo, respectively.

Less Common Adverse Reactions in IPF

Less common adverse reactions in the IPF population following administration of JASCAYD included asthenia (5% JASCAYD 18 mg twice daily, 4% JASCAYD 9 mg twice daily, and 2% placebo), amylase increased (1% JASCAYD 18 mg twice daily, 1% JASCAYD 9 mg twice daily, and 0% placebo), and vasculitis (1% JASCAYD 18 mg twice daily, 1% JASCAYD 9 mg twice daily, and 0% placebo).

Adverse Reactions for Progressive Pulmonary Fibrosis

The safety of JASCAYD was based on a randomized, placebo-controlled, double-blind trial (FIBRONEER-ILD), in which 1,178 adult patients with PPF were randomized in a 1:1:1 ratio to receive JASCAYD 9 mg twice daily, JASCAYD 18 mg twice daily, or matching placebo. Patients received JASCAYD or placebo with or without background nintedanib treatment for at least 52 weeks [see Clinical Studies (14.2)]. The median duration of exposure was 15 months in each treatment arm.

The most common adverse reactions in patients with PPF treated with JASCAYD were generally consistent with those observed in patients with IPF.

Specific Adverse Reactions of JASCAYD for PPF with or without Concomitant Use of Nintedanib

Diarrhea

Diarrhea was more common in patients using JASCAYD with concomitant nintedanib. In patients taking nintedanib, diarrhea occurred in 49%, 50%, and 37% of patients treated with JASCAYD 18 mg twice daily, JASCAYD 9 mg twice daily, and placebo, respectively. In patients without concomitant use of nintedanib, diarrhea occurred in 27%, 16%, and 16% of patients using JASCAYD 18 mg twice daily, JASCAYD 9 mg twice daily, and placebo, respectively.

Diarrhea was the most common adverse reaction associated with treatment discontinuation, and most common with JASCAYD used concomitantly with nintedanib: discontinuation occurred in 4%, 3%, and 1% in patients treated with JASCAYD 18 mg twice daily, JASCAYD 9 mg twice daily, and placebo, respectively. Diarrhea leading to treatment discontinuation occurred in 1% of patients treated with JASCAYD 18 mg twice daily and in no patients treated with JASCAYD 9 mg or placebo without concomitant use of nintedanib.

In most patients treated with JASCAYD, diarrhea was of mild to moderate intensity and generally occurred within the first 3 months of treatment.

Weight Decrease

Weight decrease was more common in patients who received JASCAYD concomitantly with nintedanib, which occurred in 12%, 10%, and 9% of patients treated with JASCAYD 18 mg twice daily, JASCAYD 9 mg twice daily, and placebo, respectively. In patients without concomitant use of nintedanib, weight decrease occurred in 13%, 8%, and 5% of patients treated with JASCAYD 18 mg twice daily, JASCAYD 9 mg twice daily, and placebo, respectively.

Malignancies

Among patients with PPF, neoplasms (benign, malignant, or unspecified) were reported in more patients with PPF treated with JASCAYD than placebo over the entire study duration of FIBRONEER-ILD (5% JASCAYD 18 mg, 5% JASCAYD 9 mg, and 3% placebo). Malignancies such as non-melanoma skin cancers and small cell lung cancer were observed in patients who received JASCAYD (basal cell carcinoma: JASCAYD 18 mg n=2 [1%] vs. JASCAYD 9 mg n=3 [1%] vs. placebo n=1 [0.3%]; squamous cell carcinoma of skin: JASCAYD 18 mg n=4 [1%] vs. JASCAYD 9 mg n=2 [0.5%] vs. placebo n=0; and small cell lung cancer: JASCAYD 18 mg n=4 [1%] vs. JASCAYD 9 mg and placebo n=0).

Less Common Adverse Reaction(s) in PPF

Less common adverse reactions in the PPF population following administration of JASCAYD include atrial fibrillation (3% JASCAYD 18 mg twice daily, 2% JASCAYD 9 mg twice daily, and <1% placebo).

7 DRUG INTERACTIONS

7.1 Effects of Other Drugs on JASCAYD

Strong CYP3A Inhibitors

Reduce the dosage of JASCAYD to 9 mg twice daily when used concomitantly with strong CYP3A inhibitors [see Dosage and Administration (2.2)].

Nerandomilast is a CYP3A substrate. Concomitant use of JASCAYD with a strong CYP3A inhibitor increases exposure of nerandomilast, which may increase the risk of JASCAYD adverse reactions [see Clinical Pharmacology (12.3)].

Moderate or Strong CYP3A Inducers

Avoid use of JASCAYD with strong or moderate CYP3A inducers.

Nerandomilast is a CYP3A substrate. Concomitant use of JASCAYD with moderate or strong CYP3A inducers is expected to decrease exposure of nerandomilast, which may decrease the efficacy of JASCAYD [see Clinical Pharmacology (12.3)].

Pirfenidone

Recommended dosage of JASCAYD is 18 mg twice daily when used concomitantly with pirfenidone. Do not reduce the dosage to 9 mg twice daily [see Dosage and Administration (2.1)].

Concomitant use of JASCAYD with pirfenidone decreases exposure of nerandomilast [see Clinical Pharmacology (12.3)]. When JASCAYD was used concomitantly with pirfenidone in patients with IPF in FIBRONEER-IPF, efficacy was not observed with the JASCAYD 9 mg twice daily dosage [see Clinical Studies (14.1)].

8 USE IN SPECIFIC POPULATIONS

8.1 Pregnancy

Risk Summary

There are no available data on JASCAYD use in pregnant women to evaluate for a drug-associated risk of major birth defects, miscarriage or other adverse maternal or fetal outcomes. There are maternal and fetal risks associated with untreated idiopathic pulmonary fibrosis (IPF) and progressive pulmonary fibrosis (PPF) during pregnancy (Clinical Considerations).

Based on findings from animal reproduction studies, JASCAYD may increase the risk for fetal loss. In an embryo-fetal development study in rats, oral administration of nerandomilast to pregnant rats during organogenesis at an exposure approximately 5 times the maximum recommended human dose (MRHD) of 36 mg/day resulted in an increase in embryo-fetal losses (see Data). Advise pregnant women and females of reproductive potential of the potential risk of fetal loss.

The estimated background risk of major birth defects and miscarriage for the indicated population is unknown. All pregnancies have a background risk of birth defect, loss, or other adverse outcomes. In the U.S. general population, the estimated background risk of major birth defects is 2% to 4% and miscarriage in clinically recognized pregnancies is 15% to 20%.

Clinical Considerations

Disease-Associated Maternal and/or Embryo/Fetal Risk

Untreated IPF or PPF can lead to respiratory failure and mortality in the mother and intrauterine growth restriction, preterm birth, fetal hypoxia, and neonatal death.

Data

Animal Data

In an embryo-fetal development study in pregnant rats dosed by the oral route during the period of organogenesis from gestation days 6 to 17, nerandomilast caused an increase in embryo-fetal losses (pre- and post-implantation loss and decreased mean number of live fetuses) at an exposure that was approximately 5 times the MRHD (on an AUC basis with a maternal oral dose of 6 mg/kg/day). Maternal toxicity, as evidenced by decreased body weight gains and adverse clinical signs, was observed at exposures approximately 7 times the MRHD (on an AUC basis with a maternal oral dose of 9 mg/kg/day). No fetal or maternal toxicities were observed at exposures up to 3 and 5 times the MRHD (on an AUC basis with maternal oral doses of 3 mg/kg/day and 6 mg/kg/day), respectively.

In an embryo-fetal development study in pregnant rabbits dosed by the oral route during the period of organogenesis from gestation days 7 to 19, no effects on maternal or fetal development were observed at an exposure that was approximately 4 times the MRHD (on an AUC basis with a maternal oral dose of 15 mg/kg/day).

In a prenatal and postnatal development study in pregnant rats dosed by the oral route during the periods of gestation and lactation from gestation day 6 to lactation day 20, nerandomilast had no effects on delivery or the growth and development of offspring at an exposure that was approximately 2 times the MRHD (on an AUC basis with a maternal oral dose of 3 mg/kg/day).

8.2 Lactation

Risk Summary

There are no data on the presence of nerandomilast or its metabolite in human milk, the effects on the breastfed infant, or the effects on milk production. Nerandomilast is present in animal milk. When a drug is present in animal milk, it is likely that the drug will be present in human milk (see Data).

The developmental and health benefits of breastfeeding should be considered along with the mother's clinical need for JASCAYD and any potential adverse effects on the breastfed infant from JASCAYD or from the underlying maternal condition.

Data

In a prenatal and postnatal development study in pregnant rats dosed by the oral route during the periods of gestation and lactation from gestation day 6 to lactation day 20, nerandomilast was present in the plasma of rat pups during the lactation period. In a single dose milk secretion study in lactating rats dosed with radiolabeled nerandomilast by the oral route, similar concentrations of total radioactivity were observed in the milk and plasma of lactating females, with the maximum radioactive concentration observed at 1 hour post dose that was significantly reduced by 24 hours post dose. The concentration of total radioactivity in animal milk does not necessarily predict the concentration of drug in human milk.

8.4 Pediatric Use

The safety and effectiveness of JASCAYD for the treatment of idiopathic pulmonary fibrosis or progressive pulmonary fibrosis have not been established in pediatric patients.

8.5 Geriatric Use

There were 930 patients 65 years of age and older in the FIBRONEER-IPF trial [see Clinical Studies (14.1)]. Of the total number of JASCAYD-treated patients with idiopathic pulmonary fibrosis in this trial, 623 (79%) were 65 years of age and older, while 251 (32%) were 75 years of age and older.

There were 733 patients 65 years of age and older in the FIBRONEER-ILD trial [see Clinical Studies (14.2)]. Of the total number of JASCAYD-treated patients with progressive pulmonary fibrosis in this trial, 490 (63%) were 65 years of age and older, while 150 (19%) were 75 years of age and older.

No overall differences in safety or effectiveness of JASCAYD have been observed between patients 65 years of age and older and younger adult patients.

8.6 Renal Impairment

JASCAYD has not been investigated in patients with end stage renal disease (eGFR <15 mL/min/1.73 m^2). Use of JASCAYD is not recommended in patients with end stage renal disease (eGFR <15 mL/min/1.73 m^2).

The recommended dosage in patients with mild (eGFR ≥60 to <90 mL/min/1.73 m^2 according to CKD-EPI), moderate (eGFR ≥30 to <60 mL/min/1.73 m^2), or severe renal impairment (eGFR ≥15 to <30 mL/min/1.73 m^2) is the same as that in patients with normal renal function [see Clinical Pharmacology (12.3)].

8.7 Hepatic Impairment

JASCAYD has not been investigated in patients with severe (Child-Pugh Class C) hepatic impairment. Use of JASCAYD is not recommended in patients with severe (Child-Pugh Class C) hepatic impairment.

The recommended dosage in patients with mild (Child-Pugh Class A) or moderate (Child-Pugh Class B) hepatic impairment is the same as that in patients with normal hepatic function [see Clinical Pharmacology (12.3)].

10 OVERDOSAGE

In the event of an overdosage with JASCAYD, monitor the patient for any signs or symptoms of adverse reactions and provide appropriate symptomatic treatment. Consider contacting the Poison Help line (1-800-222-1222) or a medical toxicologist for additional overdosage management recommendations.

11 DESCRIPTION

JASCAYD (nerandomilast tablets), for oral administration, contain nerandomilast, a phosphodiesterase 4 (PDE4) inhibitor. The chemical name of nerandomilast is [1-[[(5R)-2-[4-(5-chloropyrimidin-2-yl)-1-piperidyl]-5-oxo-6,7-dihydrothieno[3,2-d]pyrimidin-4-yl]amino]cyclobutyl]methanol. Nerandomilast has one chiral center and is the R-stereoisomer. Its structural formula is:

Nerandomilast is a white to off-white to light yellow powder with an empirical formula of C20H25ClN6O2S and a molecular weight of 449 g/mol. At or below pH 3, nerandomilast is very slightly to slightly soluble in water, and above pH 3 it is practically insoluble.

Each film-coated tablet of JASCAYD contains 9 mg or 18 mg of nerandomilast and the following inactive ingredients: croscarmellose sodium, ferric oxide red (18 mg tablets only), ferric oxide yellow (9 mg tablets only), ferrosoferric oxide (18 mg tablets only), hydroxypropyl cellulose, hypromellose, lactose monohydrate, magnesium stearate, mannitol, microcrystalline cellulose, polyethylene glycol, and talc. Each JASCAYD tablet contains less than 5 mg of sodium.

12 CLINICAL PHARMACOLOGY

12.1 Mechanism of Action

Nerandomilast is an inhibitor of phosphodiesterase 4 (PDE4) with at least nine-fold preferential inhibition of the PDE4B isoenzyme over PDE4A, PDE4C, and PDE4D based on in vitro data. PDE4 hydrolyzes and inactivates cyclic adenosine monophosphate (cAMP). Nerandomilast exerts both antifibrotic and immunomodulatory effects as PDE4B inhibition elevates intracellular cAMP levels and reduces the expression of profibrotic growth factors and inflammatory cytokines, which are overexpressed in IPF and PPF.

12.2 Pharmacodynamics

Exposure-Response

Increases in nerandomilast steady state trough concentrations were associated with better efficacy, as indicated by a smaller reduction in forced vital capacity (FVC) from baseline over 52 weeks.

Cardiac Electrophysiology

At 2.1 times the maximal concentration provided by the maximum recommended dose of nerandomilast, clinically significant QTc interval prolongation was not observed.

12.3 Pharmacokinetics

Nerandomilast exposure increased in a dose proportional manner following administration of single doses of 0.0032 to 2.6 times a single dose of 18 mg and multiple doses of 0.056 to 1 times the maximum recommended dose of 18 mg twice daily. Following administration of multiple doses of 18 mg twice daily, Cmax increases 1.3-fold and AUCtau increases 1.38-fold. Nerandomilast steady state is reached in approximately 4 days.

No clinically relevant differences in nerandomilast pharmacokinetics were observed between healthy subjects, patients with IPF, and patients with PPF.

Absorption

The absolute oral bioavailability of nerandomilast is 73%. Nerandomilast median (min, max) time to maximum plasma concentration (Tmax) is 1 to 1.25 hours (range 0.5 to 4 hours).

Effect of Food

No clinically relevant differences in nerandomilast pharmacokinetics were observed following administration with a high-fat meal (1000 calories, 50% fat).

Distribution

Nerandomilast steady state apparent (oral) central volume of distribution is 93 L (CV 37%). In vitro, nerandomilast plasma protein binding is 77% and is not concentration dependent. Nerandomilast blood-to-plasma ratio is approximately 0.6 to 0.8.

Elimination

The geometric mean (CV%) elimination half-life of nerandomilast is 17 hours (46%) with an apparent (oral) clearance of 15.2 L/h.

Metabolism

Nerandomilast is primarily metabolized by CYP3A and to a lesser extent by multiple UGT enzymes.

After oral administration of nerandomilast, chiral inversion from the pharmacologically active R-enantiomer to the pharmacologically inactive S-enantiomer occurs via metabolism. The S-enantiomer was identified as a minor metabolite of nerandomilast. The R-enantiomer is the predominant circulating enantiomer.

Excretion

After a single oral dose of radiolabeled nerandomilast, approximately 58% of the dose was recovered in feces (14% as unchanged nerandomilast) and 36% of the dose was recovered in urine (13% as unchanged nerandomilast).

Specific Populations

No clinically significant differences in the pharmacokinetics of nerandomilast were observed based on age (range: 18 to 90 years), body weight (range: 31 to 143 kg), sex, race (63% White and 35% Asian), mild (eGFR ≥60 to <90 mL/min/1.73 m^2 [calculated according to Chronic Kidney Disease Epidemiology Collaboration]), moderate (eGFR ≥30 to <60 mL/min/1.73 m^2), or severe renal impairment (eGFR ≥15 to <30 mL/min/1.73 m^2), or mild (Child-Pugh Class A) or moderate (Child-Pugh Class B) hepatic impairment.

Subjects with end stage renal disease or severe hepatic impairment (Child-Pugh Class C) have not been studied [see Use in Specific Populations (8.6, 8.7)].

Drug Interaction Studies

Strong CYP3A Inhibitors: Nerandomilast Cmax increased by 1.3-fold and AUC increased by 2.2-fold following concomitant administration with itraconazole (a strong CYP3A and P-gp inhibitor) 200 mg oral solution once daily for 4 days [see Drug Interactions (7.1)].

Pirfenidone: Nerandomilast trough concentrations at steady state (Ctrough,ss) decreased by approximately 50% following concomitant administration with pirfenidone [see Drug Interactions (7.1)].

Other Drugs: No clinically significant differences in nerandomilast Ctrough,ss were observed when used concomitantly with nintedanib. No clinically significant differences in the pharmacokinetics of the following drugs were observed when used concomitantly with nerandomilast: oral midazolam (CYP3A4 substrate), pirfenidone, and nintedanib.

In Vitro Studies

CYP450 Enzymes: Nerandomilast is a CYP3A4 substrate. Nerandomilast does not inhibit CYP3A4, CYP1A2, CYP2B6, CYP2C8, CYP2C9, CYP2C19, and CYP2D6.

Transporter Systems: Nerandomilast is a P-glycoprotein (P-gp) substrate, but is not a substrate of BCRP, OATP1B1, OATP1B3, OAT1, OAT3, and OCT2. Nerandomilast is an inhibitor of P-gp, MATE1, MATE2-K, but is not expected to cause clinically significant interactions. Nerandomilast is not an inhibitor of BCRP, OAT1, OAT3, OCT2, OATP1B1, or OATP1B3.

13 NONCLINICAL TOXICOLOGY

13.1 Carcinogenesis, Mutagenesis, Impairment of Fertility

Carcinogenesis

The carcinogenic potential of nerandomilast was assessed in Tg.rasH2 mice and Wistar Han rats. No evidence of tumorigenicity was observed in male and female Tg.rasH2 mice that received nerandomilast for 26 weeks at oral doses up to 60 and 100 mg/kg/day, respectively. No evidence of tumorigenicity was observed in male or female rats that received nerandomilast for up to 102 weeks at oral doses up to 2 mg/kg/day (approximately 2 times the MRHD on an AUC basis).

Mutagenesis

Nerandomilast was not mutagenic or clastogenic in the following assays: in vitro bacterial reverse mutation (Ames) assay, in vitro chromosomal aberration assay in human peripheral blood lymphocytes, and in vivo rat micronucleus assay.

Impairment of Fertility

Nerandomilast had no effect on fertility in male or female rats at oral doses up to 6 mg/kg/day (approximately 3 or 4 times the MRHD on an AUC basis, respectively). Decreased mating, pregnancy, and fertility indices at the highest tested dose of 9 mg/kg/day (approximately 4 or 9 times the MRHD on an AUC basis) were attributed to excessive general toxicity.

Sexually mature female monkeys administered nerandomilast by the oral route for 39 weeks showed sporadic menstrual cycle prolongation at dose levels of 10 mg/kg/day and 30 mg/kg/day (approximately 3- and 10 times the MRHD on an AUC basis, respectively). Menstrual cycles were not affected in monkeys at oral doses of 3 mg/kg/day (equivalent to the MRHD on an AUC basis).

14 CLINICAL STUDIES

14.1 Idiopathic Pulmonary Fibrosis

The efficacy of JASCAYD for idiopathic pulmonary fibrosis (IPF) was evaluated in two randomized, double-blind, placebo-controlled trials (FIBRONEER-IPF [NCT05321069] and Trial 2 [NCT04419506]).

FIBRONEER-IPF enrolled a total of 1,177 adult patients with IPF with or without background antifibrotic treatments (nintedanib or pirfenidone). They were randomized in a 1:1:1 ratio to receive JASCAYD 9 mg twice daily, JASCAYD 18 mg twice daily, or placebo twice daily until the last patient received treatment for 52 weeks (blinded trial duration up to 91 weeks; end of trial duration up to 109 weeks). Randomization was stratified by the presence or absence of background antifibrotic treatments (nintedanib or pirfenidone) at baseline. The FIBRONEER-IPF trial consisted of 83% male and 17% female patients with a mean age of 70 years (age range: 42 to 90 years). The trial population included 68% White, 32% Asian, and <1% Black or African American. For ethnicity, 8% of patients identified as Hispanic or Latino. At baseline, the mean FVC was 78% of predicted normal; 78% of the patients were on stable antifibrotic treatment (nintedanib 46%, pirfenidone 32%) and 22% were not on either treatment (15% treatment naïve, 7% previously discontinued treatment).

Trial 2 was a 12-week trial that enrolled a total of 147 adult patients with IPF with or without background antifibrotic treatments (nintedanib or pirfenidone) and were randomized 2:1 to receive JASCAYD 18 mg twice daily or placebo twice daily for 12 weeks. Randomization was stratified by the presence or absence of background antifibrotic treatments (nintedanib or pirfenidone) at baseline. The trial population in Trial 2 consisted of 77% male, and mean age of 70 years (age range: 40 to 85 years). The trial population included 78% White and 22% Asian. For ethnicity, 9% of patients identified as Hispanic or Latino. At baseline, the mean FVC was 78% of predicted normal; 50% of the patients were on stable antifibrotic treatment (nintedanib 29%, pirfenidone 21%).

In both the FIBRONEER-IPF trial and Trial 2, patients were required to have a diagnosis of IPF based on ATS/ERS/JRS/ALAT criteria. Diagnosis was confirmed by the investigator based on chest high-resolution computed tomography (HRCT) scan and, if available, lung biopsy, and usual interstitial pneumonia (UIP) or probable UIP HRCT pattern consistent with the clinical diagnosis of IPF. Patients were also required to be greater than or equal to 40 years of age with an FVC greater than or equal to 45% of predicted and a carbon monoxide diffusing capacity (DLCO, corrected for hemoglobin) greater than or equal to 25% of predicted. Prior to Visit 1 and during screening, patients had to be on stable treatment with nintedanib or pirfenidone (no dose changes for at least 12 weeks) and planned to stay on this background antifibrotic treatment after randomization. Alternatively, patients were required to be naïve to or have previously discontinued nintedanib or pirfenidone for at least 8 weeks and did not plan to start or re-start background antifibrotic treatment. Patients with active vasculitis, severe depression or suicidal behavior or ideation, or use of immunomodulatory medications (other than prednisone ≤15 mg/day or equivalent) were excluded.

Change from Baseline in Forced Vital Capacity

The primary endpoint in FIBRONEER-IPF trial was the absolute change from baseline in forced vital capacity (FVC) in milliliters (mL) at 52 weeks for JASCAYD compared with placebo.

In the FIBRONEER-IPF trial population, there was less decline in absolute change from baseline in FVC in patients who received JASCAYD compared with patients who received placebo (accounting for mortality), and this reduction in decline was statistically significant. The adjusted mean decline in patients receiving JASCAYD 18 mg or JASCAYD 9 mg was -106 mL and -122 mL, respectively, whereas in the placebo group, an adjusted mean decline of -170 mL was observed. The respective treatment differences compared with the placebo group were 64 mL (95% CI: 25, 102) and 48 mL (95% CI: 10, 86).

In the FIBRONEER-IPF trial, the results of the primary endpoint across subgroups by background antifibrotic treatment (nintedanib, pirfenidone, or none) for JASCAYD 18 mg versus placebo were consistent with the overall population. Efficacy was not observed in patients who received JASCAYD 9 mg twice daily with pirfenidone as background antifibrotic treatment [see Drug Interactions (7.1)].

Figure 1 shows the change in FVC from baseline over time in patients who received JASCAYD 18 mg twice daily compared to placebo in the FIBRONEER-IPF trial.

Figure 1 Change from Baseline in FVC (mL) in Adults with IPF over 52 weeks with JASCAYD 18 mg Compared to Placebo (FIBRONEER-IPF)

Display based on descriptive means and standard errors for change from baseline values from patients with results that were available at each week.
bid = twice daily

In Trial 2, patients taking JASCAYD 18 mg twice daily compared to placebo, with or without background antifibrotic treatments, had a reduction in FVC decline at Week 12 of 91 mL (95% CI: 44, 138).

Time To First Acute IPF Exacerbation, First Hospitalization for Respiratory Cause, Or Death

The key secondary endpoint in the FIBRONEER-IPF trial was time to first occurrence of any of the components of the composite endpoint over the blinded duration of the trial (up to 91 weeks): acute IPF exacerbation, hospitalization for respiratory cause, or death. Acute IPF exacerbation was defined as acute worsening or development of dyspnea typically less than one month duration, computed tomography with new bilateral ground-glass opacity and/or consolidation superimposed on a background pattern consistent with IPF, and deterioration not fully explained by cardiac failure or fluid overload. Neither acute IPF exacerbations nor respiratory hospitalizations were adjudicated.

Overall, there was no statistically significant treatment difference in hazard ratio (HR) for the JASCAYD 18 mg or 9 mg groups compared to placebo for the key secondary composite endpoint (JASCAYD 18 mg and 9 mg, respectively: HR 1.17 [95% CI: 0.86, 1.59] and HR 1.03 [95% CI: 0.75, 1.41]).

Survival

In the FIBRONEER-IPF trial population, the hazard ratio for all-cause mortality, assessed until the end of trial (up to 109 weeks), did not show a significant treatment difference for JASCAYD 18 mg or 9 mg compared to placebo (HR: 0.66 [95% CI: 0.41, 1.08] and HR 0.95 [95% CI: 0.61, 1.49], respectively).

Figure 2 shows the cumulative incidence of death in adults with IPF in the FIBRONEER-IPF trial for JASCAYD 18 mg and placebo.

Figure 2 Cumulative Incidence of Death over the Duration of the Trial in Adults with IPF (FIBRONEER-IPF)

bid = twice daily

14.2 Progressive Pulmonary Fibrosis

The efficacy of JASCAYD for progressive pulmonary fibrosis (PPF) was evaluated in a randomized, double-blind, placebo-controlled trial (FIBRONEER-ILD [NCT05321082]).

FIBRONEER-ILD enrolled 1,178 adult patients with PPF with or without background treatment with nintedanib. They were randomized in a 1:1:1 ratio to receive JASCAYD 9 mg twice daily, JASCAYD 18 mg twice daily, or placebo twice daily until the last patient received treatment for 52 weeks (blinded trial duration up to 109 weeks; end of trial duration up to 114 weeks). Randomization was stratified by the presence or absence of nintedanib therapy and by high resolution computed tomography (HRCT) pattern (UIP or UIP-like fibrotic pattern vs Other fibrotic patterns) using central review. The FIBRONEER-ILD trial consisted of 56% male and 44% female with a mean age of 66 years (age range: 26 to 88 years). The trial population included 58% White, 38% Asian, 1% Black or African American, 1% American Indian or Alaska Native, and 1% Multiple. For ethnicity, 14% of patients identified as Hispanic or Latino. At baseline, the mean FVC was 70% of predicted normal; 44% of the patients were on stable treatment with nintedanib and 56% of the patients were not treated with nintedanib (44% of patients were treatment naïve and 12% previously discontinued nintedanib treatment). On baseline HRCT, 71% of the patients had UIP or UIP-like fibrotic pattern and 29% of the patients had other fibrotic patterns. The underlying clinical ILD diagnoses were autoimmune ILDs (28%), hypersensitivity pneumonitis (20%), unclassifiable idiopathic interstitial pneumonia (20%), idiopathic nonspecific interstitial pneumonia (19%), and other ILDs (14%).

Patients with PPF were enrolled if they had relevant fibrosis (greater than 10% fibrotic features) on HRCT and presented with clinical signs of progression (defined as FVC decline greater than or equal to 10%, FVC decline greater than or equal to 5% and less than 10% with worsening of respiratory symptoms or imaging, or worsening of respiratory symptoms and worsening imaging all in the 24 months prior to screening). Patients were required to be greater than or equal to 18 years of age and to have an FVC greater than or equal to 45% of predicted and a DLCO (corrected for hemoglobin) greater than or equal to 25% of predicted. Prior to Visit 1 and during screening, patients had to be on stable therapy with nintedanib (no dose changes for at least 12 weeks) and planned to stay on this background PPF therapy after randomization. Alternatively, patients were required to be naïve to or have previously discontinued nintedanib for at least 8 weeks and did not plan to start or re-start background PPF treatment.

Patients were excluded from the trial if they had a pre-bronchodilator FEV1/FVC less than 0.7, acute ILD exacerbation within 3 months prior to the trial, active vasculitis within 8 weeks prior to the trial, a history of suicidal behavior or ideation, or severe depression. Patients were also excluded if they were being treated with the following medications prior to the trial: prednisone >15 mg/day or equivalent within 4 weeks; cyclophosphamide, tocilizumab, mycophenolate, pirfenidone within 8 weeks; rituximab within 6 months.

Change from Baseline in Forced Vital Capacity

The primary endpoint in FIBRONEER-ILD trial was the absolute change from baseline in forced vital capacity (FVC) in mL at 52 weeks for JASCAYD compared with placebo.

In the FIBRONEER-ILD trial population, there was less decline in absolute change from baseline in FVC in patients who received JASCAYD compared with patients who received placebo (accounting for mortality), and this reduction in decline was statistically significant. The adjusted mean decline in patients receiving JASCAYD 18 mg or JASCAYD 9 mg was -86 mL and -69 mL, respectively, whereas in the placebo group, an adjusted mean decline of -152 mL was observed. The respective treatment difference compared with the placebo group was 65 mL (95% CI: 30, 101) and 83 mL (95% CI: 48, 118). FVC results across relevant subgroups were similar. See Figure 3.

Figure 3 Absolute Change from Baseline in FVC (mL) at 52 Weeks for JASCAYD 18 mg versus Placebo (FIBRONEER-ILD)

These results are from an exploratory analysis. Values shown here are for descriptive purposes. Includes values from patients with results at Week 52, last observed value for patients who had a lung transplant or died before Week 52, and imputed Week 52 values for all other patients with missing data.
bid = twice daily

Figure 4 shows the change in FVC from baseline over time patients receiving JASCAYD 18 mg twice daily compared to placebo in the FIBRONEER-ILD trial.

Figure 4 Change from Baseline in FVC (mL) in Adults with PPF over 52 Weeks with JASCAYD 18 mg Compared to Placebo (FIBRONEER-ILD)

Display based on descriptive means and standard errors for change from baseline values from patients with results that were available at each week.
bid = twice daily

Time To First Acute ILD Exacerbation, First Hospitalization for Respiratory Cause, Or Death

The key secondary endpoint in the FIBRONEER-ILD trial was the time to the first occurrence of any of the components of the composite endpoint over the blinded duration of the trial (up to 109 weeks): acute ILD exacerbation, hospitalization for respiratory cause, or death. Acute ILD exacerbation was defined as acute worsening or development of dyspnea typically less than 1 month duration, computed tomography with new bilateral ground-glass opacity and/or consolidation superimposed on a background pattern consistent with fibrosing ILD, and deterioration not fully explained by cardiac failure or fluid overload. Neither acute ILD exacerbations nor respiratory hospitalizations were adjudicated.

Overall, there was no statistically significant treatment difference in the hazard ratio (HR) for the JASCAYD 18 mg or 9 mg groups compared to placebo for the key secondary composite endpoint (JASCAYD 18 mg or 9 mg groups, respectively, compared to placebo: HR 0.77 (95% CI: 0.59, 1.01) and HR 0.88 (95% CI: 0.68, 1.14).

See Figure 5 for results of JASCAYD 18 mg versus placebo for the key secondary endpoint and its components over the blinded duration of the FIBRONEER-ILD trial.

Figure 5 Acute ILD Exacerbation, Hospitalization for Respiratory Cause or Death over the Blinded Duration of the Trial (FIBRONEER-ILD)a

Results for the components of the key secondary endpoint are exploratory. Values shown here are for descriptive purposes.

a Blinded trial duration was up to 109 weeks.
bid = twice daily

Survival

In the FIBRONEER-ILD trial population, the hazard ratios for all-cause mortality, assessed until the end of trial (up to 114 weeks), for JASCAYD 18 mg and 9 mg compared to placebo were 0.51 [95% CI: 0.34, 0.78] and 0.51 [95% CI: 0.34, 0.78], respectively. These results were not prespecified for multiplicity control.

Figure 6 shows the cumulative incidence of death in adults with PPF in the FIBRONEER-ILD trial for JASCAYD 18 mg and placebo.

Figure 6 Cumulative Incidence of Death over the Duration of the Trial in Adults with PPF (FIBRONEER-ILD)

bid = twice daily

16 HOW SUPPLIED/STORAGE AND HANDLING

How Supplied

JASCAYD tablets are supplied as follows:

Tablet Strength | Tablet Description | Package Configuration | NDC
9 mg | light yellow, oval, biconvex, film-coated tablets debossed with the Boehringer Ingelheim company symbol on one side and "F9" on the other side | Bottles of 60 with child-resistant closure | 0597-2465-41
18 mg | light red, oval, biconvex, film-coated tablets debossed with the Boehringer Ingelheim company symbol on one side and "F18" on the other side | Bottles of 60 with child-resistant closure | 0597-7313-21

Storage and Handling

Store at 20°C to 25°C (68°F to 77°F); excursions permitted to 15°C to 30°C (59°F to 86°F) [see USP Controlled Room Temperature]. Store in the original container to protect from light.

17 PATIENT COUNSELING INFORMATION

Advise the patient to read the FDA-approved patient labeling (Patient Information).

Pregnancy

Advise female patients to contact their healthcare provider if they become pregnant or suspect they may be pregnant during treatment with JASCAYD. Advise female patients of the potential risk of fetal loss [see Use in Specific Populations (8.1)].

Missed Dose

Inform patients that if they miss a dose of JASCAYD, they should take the next dose at the next scheduled time. Advise patients to not make up for a missed dose or exceed the recommended dosage of 18 mg twice daily [see Dosage and Administration (2.1)].

Distributed by:
Boehringer Ingelheim Pharmaceuticals, Inc.
Ridgefield, CT 06877 USA

Licensed from:
Boehringer Ingelheim International GmbH, Ingelheim, Germany

JASCAYD is a registered trademark of and used under license from Boehringer Ingelheim International GmbH.

Copyright © 2025 Boehringer Ingelheim International GmbH
ALL RIGHTS RESERVED

COL11694CL182025
SPL14534D

PATIENT INFORMATION
JASCAYD® (JASS-kayd)
(nerandomilast tablets)
for oral use

What is JASCAYD?
JASCAYD is a prescription medicine used:

- to treat adults with a lung disease called idiopathic pulmonary fibrosis (IPF).
- to treat adults with a lung disease called progressive pulmonary fibrosis (PPF).

It is not known if JASCAYD is safe and effective in children.

Before you take JASCAYD, tell your healthcare provider about all of your medical conditions, including if you:

- have kidney problems.
- have liver problems.
- are pregnant or plan to become pregnant. JASCAYD may cause loss of your pregnancy (miscarriage). It is not known if JASCAYD can harm your unborn baby. Tell your healthcare provider right away if you become pregnant or think you are pregnant while taking JASCAYD.
- are breastfeeding or plan to breastfeed. It is not known if JASCAYD passes into your breastmilk. You and your healthcare provider should decide if you will take JASCAYD or breastfeed.

Tell your healthcare provider about all the medicines you take, including prescription and over-the-counter medicines, vitamins, and herbal supplements. JASCAYD may affect the way other medicines work, and other medicines may affect how JASCAYD works. Know the medicines you take. Keep a list of them and show it to your healthcare provider or pharmacist when you get a new medicine.

How should I take JASCAYD?

- Take JASCAYD exactly as your healthcare provider tells you to take it.
- Your healthcare provider will tell you how much JASCAYD to take and when to take it.
- Take JASCAYD either with or without food.
- Swallow JASCAYD tablets whole.
- If you cannot swallow JASCAYD tablets whole:
  - Place 3 to 4 ounces (about 100 mL) of non-carbonated, room temperature water in a glass. Do not use any other liquids.
  - Place a JASCAYD tablet in the water, without crushing the tablet, and stir regularly for about 15 to 20 minutes until the tablet is in very small pieces (the tablet will not completely dissolve).
  - Drink the JASCAYD and water mixture within 2 hours of mixing.
  - If you do not drink the mixture right away, stir the mixture again before drinking.
  - Rinse the glass with 3 to 4 ounces (about 100 mL) of water and drink to make sure that you have taken the full dose of JASCAYD.
- If you miss a dose of JASCAYD, take your next dose at your regular time. Do not take the missed dose.
- Do not take more than two 18 mg JASCAYD tablets in 1 day.
- If you take too much JASCAYD, call your healthcare provider or Poison Help line at 1-800-222-1222, or go to the nearest hospital emergency room right away.

What are the possible side effects of JASCAYD?
The most common side effects of JASCAYD include:

- diarrhea
- COVID-19
- upper respiratory tract infection
- depression

- weight loss
- decreased appetite
- nausea
- fatigue

- headache
- vomiting
- back pain
- dizziness

These are not all of the possible side effects of JASCAYD. For more information, ask your healthcare provider or pharmacist. Call your doctor for medical advice about side effects. You may report side effects to FDA at 1-800-FDA-1088.

How should I store JASCAYD?

- Store JASCAYD at room temperature between 68°F to 77°F (20°C to 25°C).
- Store JASCAYD in the original child-resistant container to protect it from light.

Keep JASCAYD and all medicines out of the reach of children.

General information about the safe and effective use of JASCAYD.
Medicines are sometimes prescribed for purposes other than those listed in a Patient Information leaflet. Do not use JASCAYD for any condition for which it was not prescribed. Do not give JASCAYD to other people, even if they have the same symptoms you have. It may harm them. You can ask your healthcare provider or pharmacist for information about JASCAYD that is written for health professionals.

What are the ingredients in JASCAYD?
Active ingredient: nerandomilast
Inactive ingredients: croscarmellose sodium, ferric oxide red (18 mg tablets only), ferric oxide yellow (9 mg tablets only), ferrosoferric oxide (18 mg tablets only), hydroxypropyl cellulose, hypromellose, lactose monohydrate, magnesium stearate, mannitol, microcrystalline cellulose, polyethylene glycol, and talc. Each tablet contains less than 5 mg of sodium.

Distributed by: Boehringer Ingelheim Pharmaceuticals, Inc., Ridgefield, CT 06877 USA
Licensed from: Boehringer Ingelheim International GmbH, Ingelheim, Germany
JASCAYD is a registered trademark of and used under license from Boehringer Ingelheim International GmbH.
Copyright © 2025 Boehringer Ingelheim International GmbH ALL RIGHTS RESERVED
COL11694CL182025
For more information about JASCAYD, including current Prescribing Information and patient support, go to www.jascayd.com or call Boehringer Ingelheim Pharmaceuticals, Inc. at 1-800-542-6257, or scan the code to go to www.jascayd.com.

This Patient Information has been approved by the U.S. Food and Drug Administration.

Revised: 12/2025

PRINCIPAL DISPLAY PANEL - 9 mg Tablet Bottle Carton

NDC 0597-2465-41

Jascayd®
(nerandomilast tablets)

9 mg

Rx only

60 tablets

Boehringer
Ingelheim

PRINCIPAL DISPLAY PANEL - 18 mg Tablet Bottle Carton

NDC 0597-7313-21

Jascayd®
(nerandomilast tablets)

18 mg

Rx only

60 tablets

Boehringer
Ingelheim